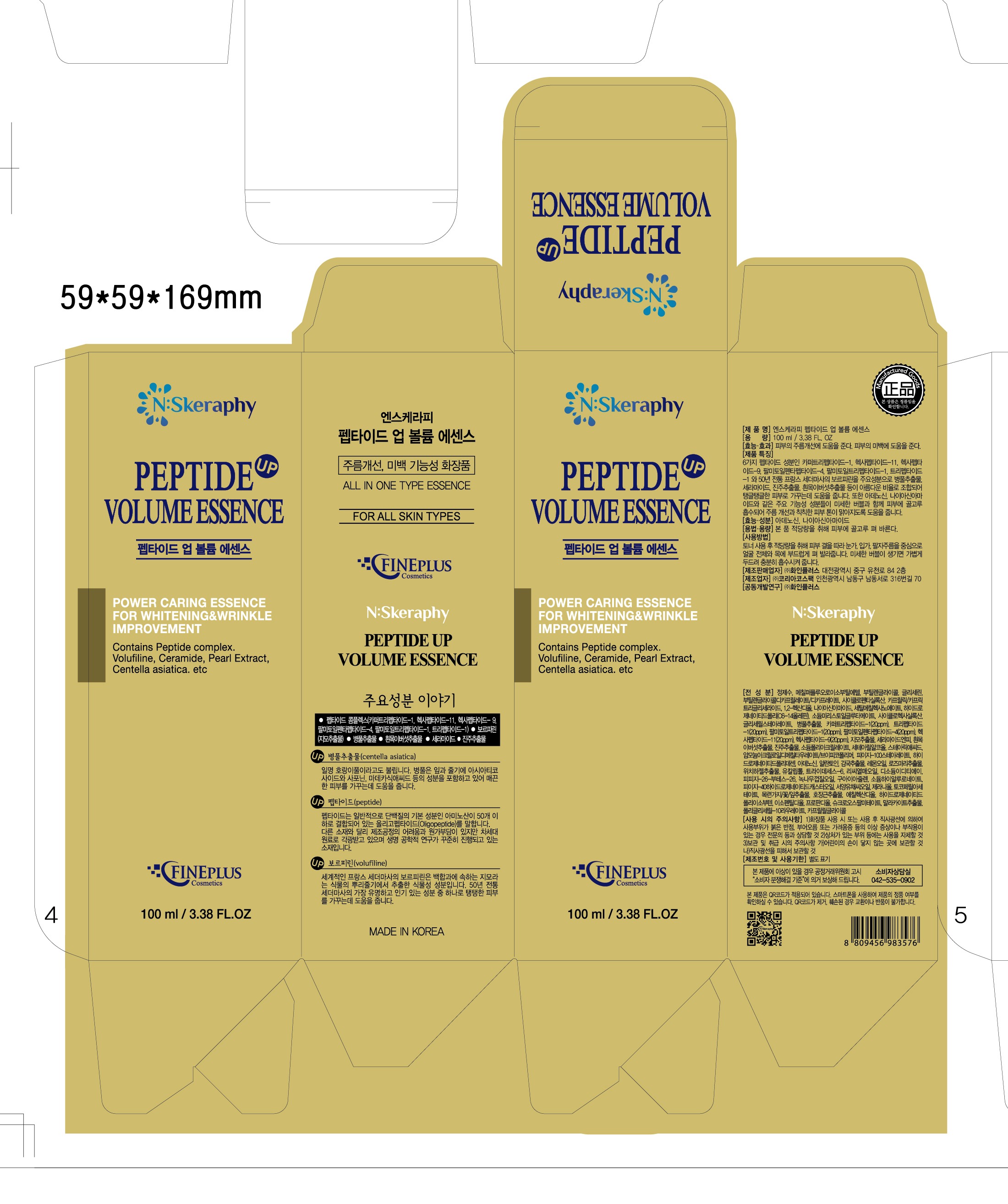 DRUG LABEL: PEPTIDE UP VOLUME ESSENCE
NDC: 71774-0001 | Form: CREAM
Manufacturer: FINEPLUS Co.,Ltd.
Category: otc | Type: HUMAN OTC DRUG LABEL
Date: 20171003

ACTIVE INGREDIENTS: NIACINAMIDE 2 g/100 mL; ADENOSINE 0.04 g/100 mL
INACTIVE INGREDIENTS: GLYCERIN; WATER

FINEPLUS Co.,Ltd.

ACTIVE INGREDIENT

Niacinamide, Adenosine

INACTIVE INGREDIENT

Water, Glycerin, Etc

PURPOSE

Whitetning, Anti-Wrinkle

keep out of reach of the children

INDICATIONS AND USAGE

1. Pump appropriate amount and apply softly all over your face.
2. Wait approximately 30 seconds until oxygen bubbles foam up.
3. Tap lightly as if you're massaging for better absorption when oxygen bubbles die down naturally.

WARNINGS

1. Do not use in the following cases(Eczema and scalp wounds)
2.Side Effects
1)Due to the use of this druf if rash, irritation, itching and symptopms of hypersnesitivity occur dicontinue use and consult your phamacisr or doctor
3.General Precautions
1)If in contact with the eyes, wash out thoroughty with water If the symptoms are servere, seek medical advice immediately
2)This product is for exeternal use only. Do not use for internal use
4.Storage and handling precautions
1)If possible, avoid direct sunlight and store in cool and area of low humidity
2)In order to maintain the quality of the product and avoid misuse
3)Avoid placing the product near fire and store out in reach of children

DOSAGE AND ADMINISTRATION

for external use only